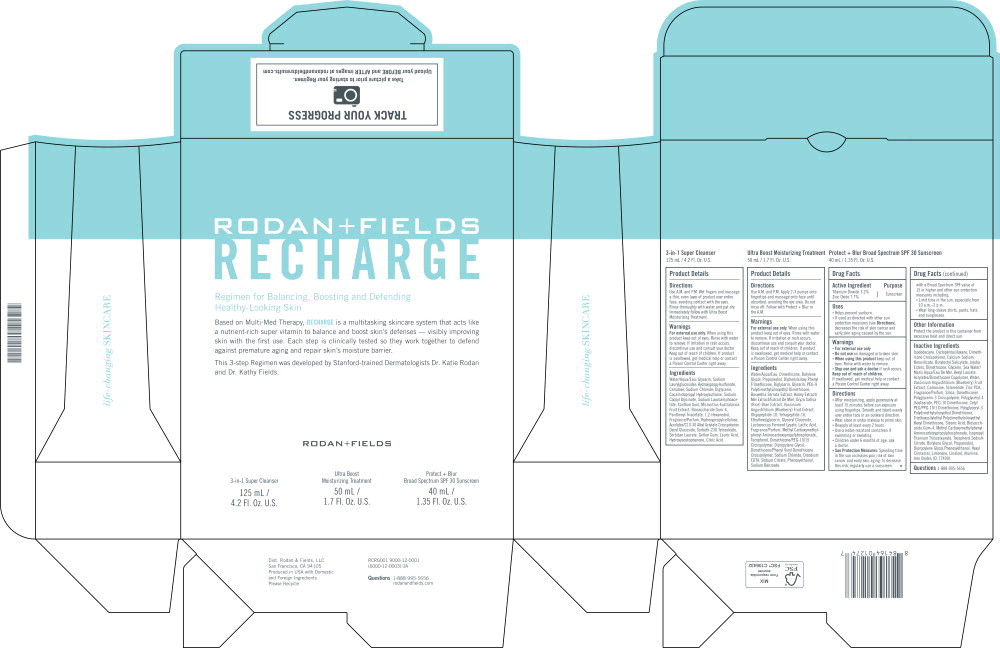 DRUG LABEL: RECHARGE Regimen for Balancing, Boosting and Defending Healthy-Looking skin
NDC: 14222-8000 | Form: CREAM
Manufacturer: Rodan & Fields
Category: otc | Type: HUMAN OTC DRUG LABEL
Date: 20231204

ACTIVE INGREDIENTS: TITANIUM DIOXIDE 0.032 g/1 mL; ZINC OXIDE 0.077 g/1 mL
INACTIVE INGREDIENTS: ISODODECANE; CYCLOMETHICONE 5; BOROSILICATE GLASS; BUTYLOCTYL SALICYLATE; HYDROGENATED JOJOBA OIL/JOJOBA OIL, RANDOMIZED (IODINE VALUE 64-70); DIMETHICONE; GLYCERIN; WATER; HEXYL LAURATE; PROPANEDIOL; POLYGLYCERYL-4 ISOSTEARATE; BUTYLENE GLYCOL; STEARIC ACID; ALUMINUM OXIDE; ZINC PIDOLATE; SCLAREOLIDE; CARNOSINE; SILICON DIOXIDE; LOWBUSH BLUEBERRY; PHENOXYETHANOL; LINALOOL, (+/-)-; BIOSACCHARIDE GUM-4; FERRIC OXIDE RED; DIPROPYLENE GLYCOL; .ALPHA.-HEXYLCINNAMALDEHYDE; LIMONENE, (+)-; SODIUM CITRATE, UNSPECIFIED FORM; CETYL PEG/PPG-10/1 DIMETHICONE (HLB 3); TOCOPHEROL; ISOPROPYL TITANIUM TRIISOSTEARATE

Drug Facts

Active Ingredient

Titanium Dioxide 3.2%

Zinc Oxide 7.7%

Purpose

Sunscreen

Sunscreen

Uses

- Helps prevent sunburn.
- If used as directed with other sun protection measures (see Directions), decreases the risk of skin cancer and early skin aging caused by the sun.

Warnings

- For external use only

- Do not use on damaged or broken skin.

- When using this product keep out of eyes. Rinse with water to remove.

- Stop use and ask a doctor if rash occurs.

Keep out of reach of children.

If swallowed, get medical help or contact a Poison Control Center right away.

Directions

- After moisturizing, apply generously at least 15 minutes before sun exposure using fingertips. Smooth and blend evenly over entire face in an outward direction.
- Wear alone or under makeup to prime skin.
- Reapply at least every 2 hours.
- Use a water-resistant sunscreen if swimming or sweating.
- Children under 6 months of age: ask a doctor.
- Sun Protection Measures: Spending time in the sun increases your risk of skin cancer and early skin aging. To decrease this risk, regularly use a sunscreen with a Broad Spectrum SPF value of 15 or higher and other sun protection measures including:
  - Limit time in the sun, especially from 10 a.m.-2 p.m.
  - Wear long-sleeve shirts, pants, hats and sunglasses.

Other Information

Protect the product in this container from excessive heat and direct sun.

Inactive Ingredients

Isododecane, Cyclopentasiloxane, Dimethicone Crosspolymer, Calcium Sodium Borosilicate, Butyloctyl Salicylate, Jojoba Esters, Dimethicone, Glycerin, Sea Water/Maris Aqua/Eau De Mer, Hexyl Laurate, Acrylates/Dimethicone Copolymer, Water, Vaccinium Angustifolium (Blueberry) Fruit Extract, Carnosine, Sclareolide, Zinc PCA, Fragrance/Parfum, Silica, Dimethicone/Polyglycerin-3 Crosspolymer, Polyglyceryl-4 Isostearate, PEG-10 Dimethicone, Cetyl PEG/PPG-10/1 Dimethicone, Polyglyceryl-3 Polydimethylsiloxyethyl Dimethicone, Triethoxysilylethyl Polydimethylsiloxyethyl Hexyl Dimethicone, Stearic Acid, Biosaccharide Gum-4, Methyl Carboxymethylphenyl Aminocarboxypropylphosphonate, Isopropyl Titanium Triisostearate, Tocopherol, Sodium Citrate, Butylene Glycol, Propanediol, Dipropylene Glycol, Phenoxyethanol, Hexyl Cinnamal, Limonene, Linalool, Alumina, Iron Oxides (Cl 77499).

Questions

1-888-995-5656

Principal Display Panel - Carton Label

RODAN + FIELDS
RECHARGE

Regimen for Balancing, Boosting and Defending

Healthy-Looking Skin

Based on Multi-Med Therapy, RECHARGE is a multitasking skincare system that acts like a nutrient-rich super vitamin to balance and boost skin's defenses — visibly improving skin with the first use. Each step is clinically tested so they work together to defend against premature aging and repair skin's moisture barrier.

This 3-step Regimen was developed by Stanford-trained Dermatologists Dr. Katie Rodan and Dr. Kathy Fields.

RDDAN + FIELDS

3-in-1 Super Cleanser

125 mL / 4.2 Fl. Oz. U.S.

Ultra Boost

Moisturizing Treatment

50 mL / 1.7 FI. Oz. U.S.

Protect + Blur

Broad Spectrum SPF 30 Sunscreen

40 mL / 1.35 FI. Oz. U.S.